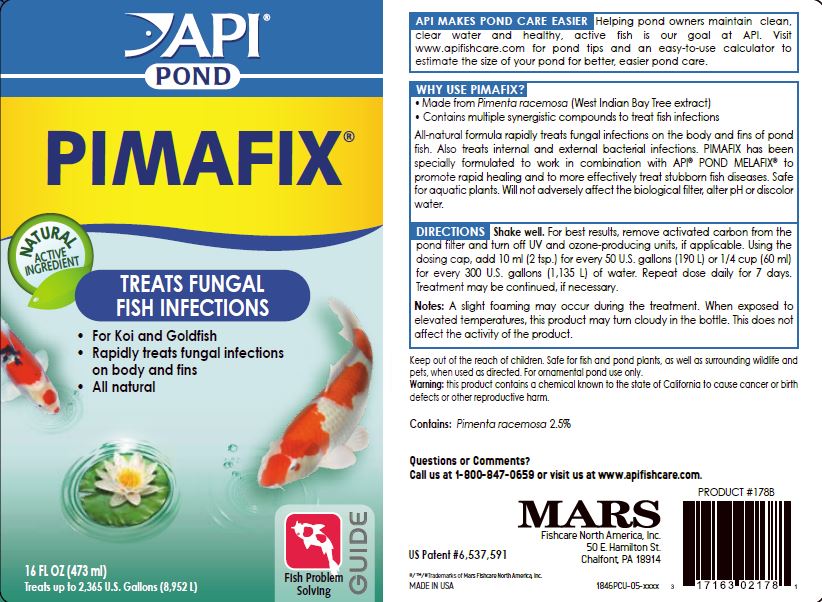 DRUG LABEL: API POND PIMAFIX
NDC: 17163-178 | Form: LIQUID
Manufacturer: MARS FISHCARE NORTH AMERICA, INC.
Category: animal | Type: OTC ANIMAL DRUG LABEL
Date: 20191219

ACTIVE INGREDIENTS: BAY OIL (PIMENTA RACEMOSA) 2.5 g/100 mL

Drug Label

DIRECTIONS

Shake well.

For best results, remove activated carbon from the pond filter and turn off UV and ozone- producing units, if applicable.

Using the dosing cap, add 10 ml (2 tsp.) for every 50 U.S. gallons (190 L) or 1/4 cup (60 ml) for every 300 U.S. gallons (1,135 L) of water.

Repeat dose daily for 7 days.

Treatment may be continued, if necessary.

Notes: A slight foaming may occur during the treatment. When exposed to elevated temperatures, this product may turn cloudy in the bottle. This does not affect the activity of the product.

Keep out of reach of children. Safe for fish and pond plants, as well as surrounding wildlife and pets, when used as directed. For ornamental pond use only.

Warning: this product contains a chemical known to the state of California to cause cancer or birth defects or other reproductive harm.

ACTIVE INGREDIENT

Contains: Pimenta racemosa 2.5%

Questions or Comments?

Call us at 1-800-847-0659 or visit us at www.apifishcare.com.

DESCRIPTION

API MAKES POND CARE EASIER

Helping pond owners maintain clean, clear water and healthy, active fish is our goal at API.

Visit www.apifishcare.com for pond tips and an eazy-to-use calculator to estimate the size of your pond for better, easier pond care.

INDICATIONS AND USAGE

WHY USE PIMAFIX?

Made from Pimenta racemosa (West Indian Bay Tree extract)

Contains multiple synergistic compounds to treat fish infections

All-natural formula rapidly treats fungal infections on the body and fins of pond fish.

Also treats internal and external bacterial infections.

PIMAFIX has been specially formulated to work in combination with API POND MELAFIX to promote rapid healing and to more effectively treat stubborn fish diseases.

Safe for aquatic plants.

Will not adversely affect the biological filter, alter pH or discolor water.

PACKAGE LABEL

API

POND

PIMAFIX

NATURAL

ACTIVE

INGREDIENT

TREATS FUNGAL

FISH INFECTIONS

For Koi and Goldfish

Rapidly treats fungal infections

on body and fins

All natural

GUIDE

Fish Problem

Solving

16 FL OZ (437 mL)

Treats up to 2,365 U.S. Gallons (8,952 L)